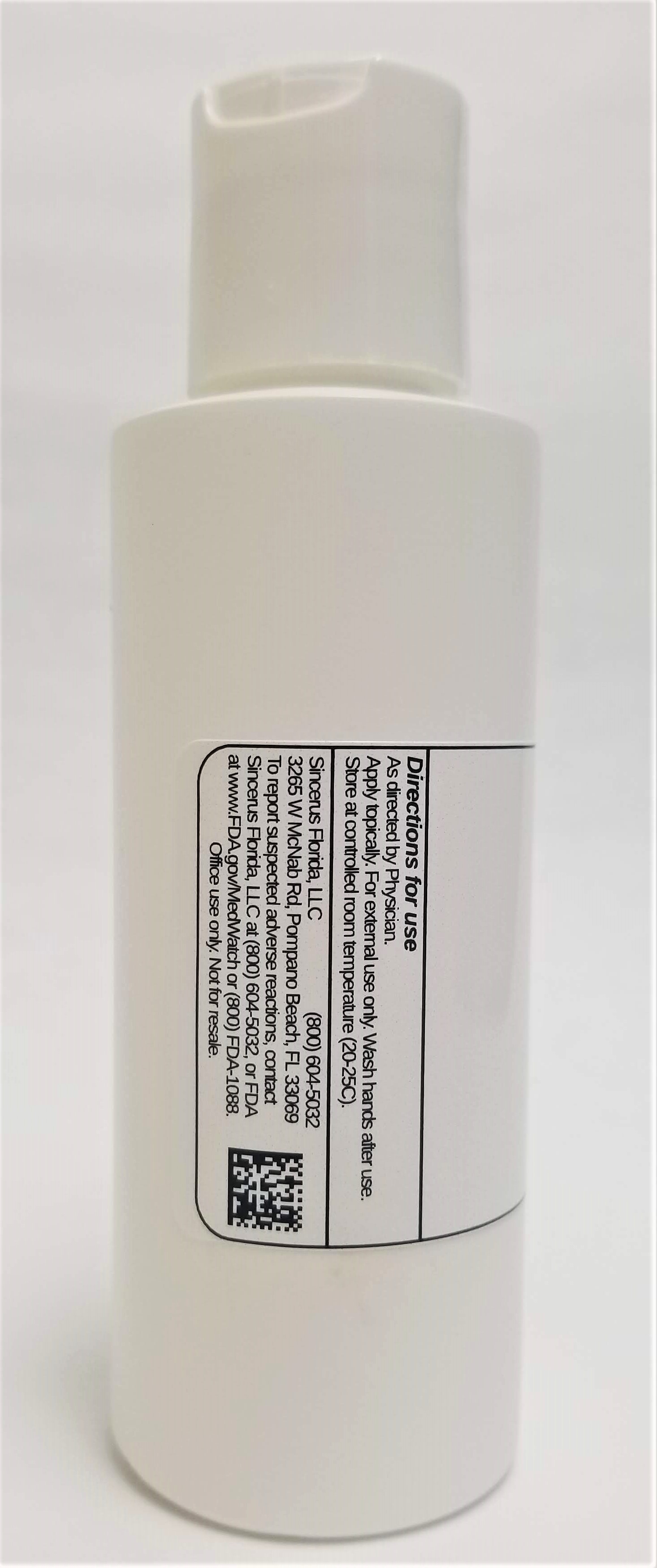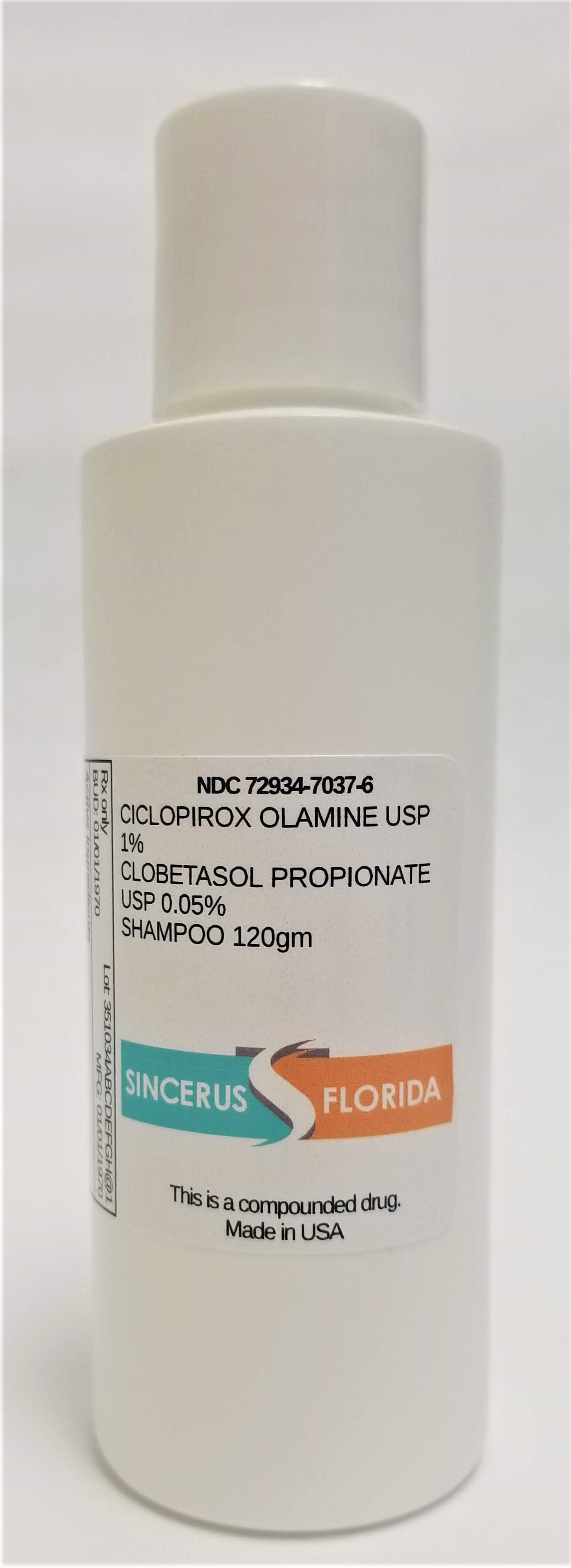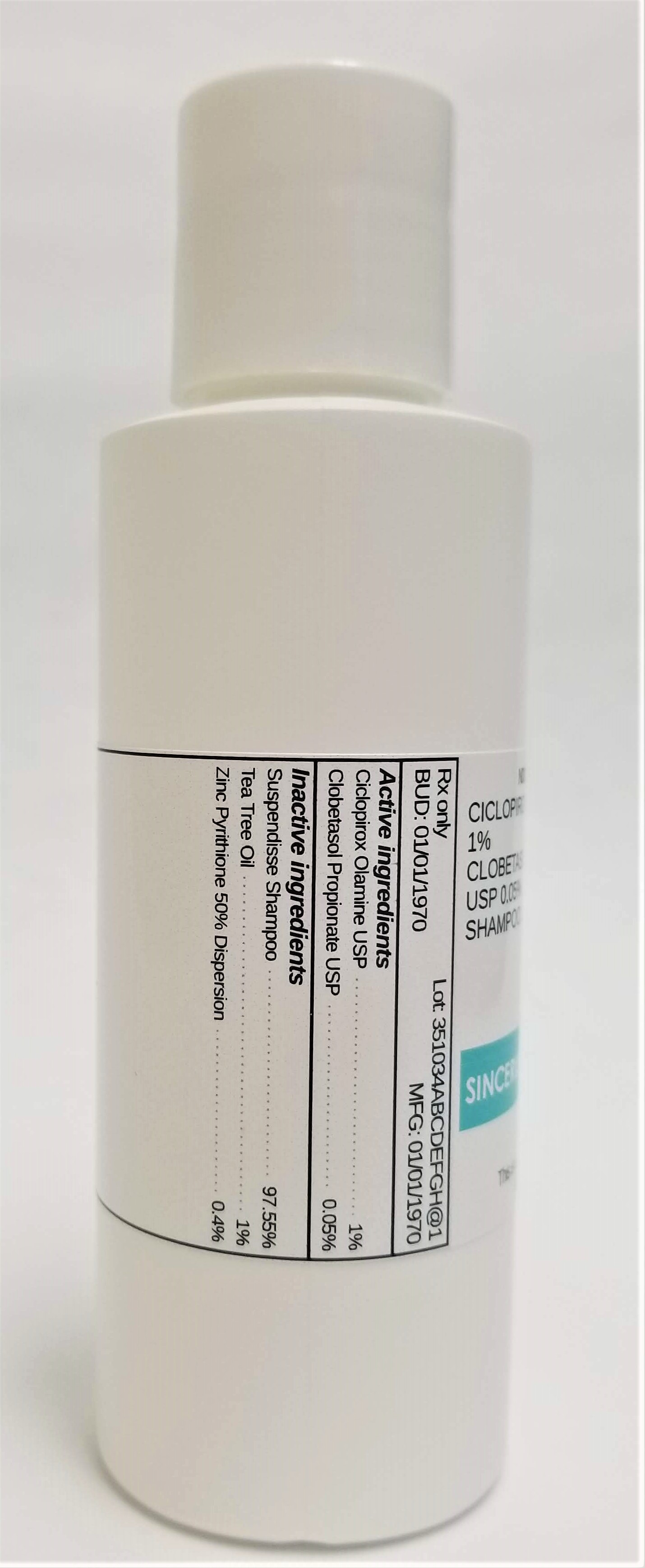 DRUG LABEL: CICLOPIROX 1% / CLOBETASOL PROPIONATE 0.05%
NDC: 72934-7037 | Form: SHAMPOO
Manufacturer: Sincerus Florida, LLC
Category: prescription | Type: HUMAN PRESCRIPTION DRUG LABEL
Date: 20190424

ACTIVE INGREDIENTS: CICLOPIROX 1 g/100 g; CLOBETASOL PROPIONATE 0.05 g/100 g

CICLOPIROX 1% / CLOBETASOL PROPIONATE 0.05%